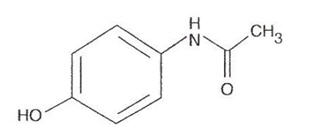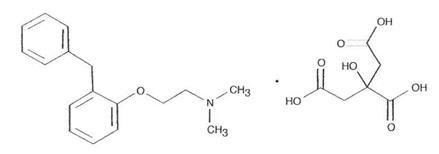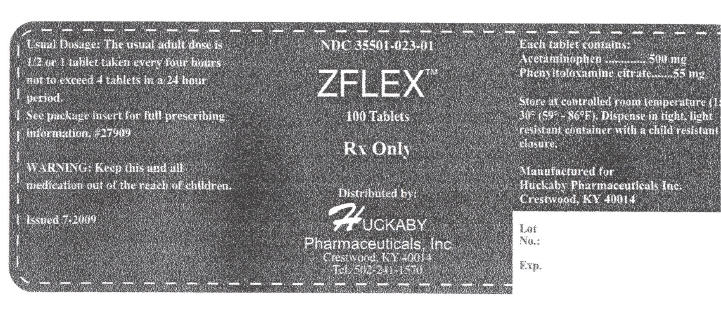 DRUG LABEL: ZFLEX
NDC: 35501-023 | Form: TABLET
Manufacturer: Huckaby Pharmaceuticals, Inc.
Category: prescription | Type: HUMAN PRESCRIPTION DRUG LABEL
Date: 20100412

ACTIVE INGREDIENTS: Acetaminophen 500 mg/1 1; Phenyltoloxamine Citrate 55 mg/1 1
INACTIVE INGREDIENTS: povidone; cellulose, microcrystalline; magnesium stearate

NDC 35501-023-01
ZFLEX
ACETAMINOPHEN
AND
PHENYLTOLOXAMINE
TABLETS, USP

Rx Only

DESCRIPTION

Each Tablet Contains:

Acetaminophen | 500 mg

Phenyltoloxamine Citrate | 55 mg

Acetaminophen, 4'-hydroxyacetanilide, a slightly bitter, white odorless, crystalline powder, is a non-opiate, non-salicylate analgesic and antipyretic.

Phenyltoloxamine citrate is an antihistamine having the chemical name N, N-dimethyl-2-(α-phenyl-o-tolyloxy) ethylamine dihydrogen citrate.

Inactive ingredients: Each tablet contains povidone, microcrystalline cellulose, sodium starch glycolate and magnesium stearate.

CLINICAL PHARMACOLOGY

The analgesic action of acetaminophen involves peripheral influences, but the specific mechanism is as yet undetermined. Antipyretic activity is mediated through hypothalamic heat regulating centers. Acetaminophen inhibits prostaglandin synthetase. Therapeutic doses of acetaminophen have negligible effects on the cardiovascular or respiratory systems; however, toxic doses may cause circulatory failure and rapid, shallow breathing.

Pharmacokinetics

The behavior of the individual components is described below.

Acetaminophen

Acetaminophen is rapidly absorbed from the gastrointestinal tract and is distributed throughout most body tissues. The plasma half-life is 1.25 to 3 hours, but may be increased by liver damage and following overdosage. Elimination of acetaminophen is principally by liver metabolism (conjugation) and subsequent renal excretion of metabolites. Approximately 85% of an oral dose appears in the urine within 24 hours of administration, most as the glucuronide conjugate, with small amounts of other conjugates and unchanged drug.

See OVERDOSAGE for toxicity information.

Phenyltoloxamine Citrate

Phenyltoloxamine is an H1 blocking agent which interferes with the action of histamine primarily in capillaries surrounding mucous tissues and sensory nerves of the nasal and adjacent areas. It has the ability to interfere with certain areas of acetylcholine-inhibiting secretions in the nose, mouth and pharynx. It commonly causes CNS depression.

INDICATIONS AND USAGE

For the temporary relief of minor aches and pains associated with headaches, backache, muscular aches, the menstrual and premenstrual periods, colds, the flu, toothaches, as well as for minor pain from arthritis, and to reduce fever.

CONTRAINDICATIONS

This product should not be administered to patients who have previously exhibited hypersensitivity to acetaminophen or phenyltoloxamine citrate.

PRECAUTIONS

Laboratory Tests

In patients with severe hepatic or renal disease, effects of therapy should be monitored with serial liver and/or renal function tests.

Drug/Laboratory Test Interactions

Acetaminophen may produce false-positive test results for urinary 5-hydroxyindoleacetic acid. The sedative effects of phenyltoloxamine citrate are additive to the CNS depressant effects of alcohol, hypnotics, sedatives and tranquilizers.

Carcinogenesis, Mutagenesis, Impairment of Fertility

No adequate studies have been conducted in animals to determine whether phenyltoloxamine citrate or acetaminophen has a potential for carcinogenesis, mutagenesis, or impairment of fertility.

Pregnancy

Teratogenic Effects

Pregnancy Category C

There are no adequate and well-controlled studies in pregnant women. Use during pregnancy only if the potential benefit justifies the potential risk to the fetus.

Nursing Mothers

Acetaminophen is excreted in breast milk in small amounts, but the significance of its effects on nursing infants is not known. Because many drugs are excreted in human milk and because of the potential for serious adverse reactions in nursing infants from phenyltoloxamine citrate and acetaminophen, a decision should be made whether to discontinue nursing or to discontinue the drug, taking into account the importance of the drug to the mother.

Pediatric Use

Safety and effectiveness in the pediatric population have not been established.

ADVERSE REACTIONS

Dermatological: skin rash, pruritus.

The following adverse drug events may be borne in mind as potential effects of acetaminophen: allergic reactions, rash, thrombocytopenia, agranulocytosis.

OVERDOSAGE

Following an acute overdosage, toxicity may result from phenyltoloxamine citrate or acetaminophen.

Acetaminophen

In acetaminophen overdosage: dose-dependent, potentially fatal hepatic necrosis is the most serious adverse effect. Renal tubular necrosis, hypoglycemic coma, and thrombocytopenia may also occur.

Early symptoms following a potentially hepatotoxic overdose may include: nausea, vomiting, diaphoresis and general malaise. Clinical and laboratory evidence of hepatic toxicity may not be apparent until 48 to 72 hours post-ingestion.

In adults, hepatic toxicity has rarely been reported with acute overdoses of less than 10 grams, or fatalities with less than 15 grams.

Treatment

A single or multiple overdose with phenyltoloxamine citrate or acetaminophen is a potentially lethal overdose, and consultation with a regional poison control center is recommended. Immediate treatment includes support of cardiorespiratory function and measures to reduce drug absorption. Vomiting should be induced mechanically, or with syrup of ipecac, if the patient is alert (adequate pharyngeal and laryngeal reflexes).

If the dose of acetaminophen may have exceeded 140 mg/kg, acetylcysteine should be administered as early as possible. Serum acetaminophen levels should be obtained, since levels four or more hours following ingestion help predict acetaminophen toxicity. Do not await acetaminophen assay results before initiating treatment. Hepatic enzymes should be obtained initially, and repeated at 24-hour intervals. Methemoglobinemia over 30% should be treated with methylene blue by slow intravenous administration. The toxic dose for adults for acetaminophen is 10 g.

Dosage

Adults 12 years and over - ½ or 1 tablet every 4 hours.
Maximum daily dose - 5 tablets.
Children 6 to under 12 years - ½ tablet every 4 hours.
Maximum daily dose - 2½ tablets
Children under 6 years of age: consult a physician.

WARNINGS

Do not take this product for pain for more than 10 days (adults) or 5 days (children), and do not take for fever for more than 3 days unless directed by a physician. If pain or fever persists, if new symptoms occur, or if redness or swelling is present, consult a physician immediately because these could be signs of a serious condition. Do not give this product to children under 12 years of age for the pain of arthritis unless directed by a physician. May cause drowsiness; alcohol, sedatives and tranquilizers may increase the drowsiness effect. Avoid alcoholic beverages while taking this product. Do not take this product if you are taking sedatives or tranquilizers without first consulting your physician. Use caution when driving a motor vehicle or operating machinery.

Keep this and all drugs out of the reach of children. In case of accidental overdose, seek professional assistance or contact a Poison Control Center immediately. Prompt medical attention is critical, for adults as well as for children, even if you do not notice any signs or symptoms. As with any drug, if you are pregnant or nursing a baby, seek the advice of a health professional before using this product.

STORAGE AND HANDLING

STORE AT ROOM TEMPERATURE 15°-30°C (59°-86°F), AVOID EXCESSIVE HEAT.

HOW SUPPLIED

NDC# 35501-023-01 Bottles of 100 count tablets; and samples NDC# 35501-023-02 containing 4 tablets. A red capsule shaped tablet with a score on both sides. Both sides with "ZFLEX" on the left side of the score and a blank space on the right side of the score. If tablet is broken at the score, one side will display "ZFLEX" and the other side will be blank.

Rx only

Manufactured for:
Huckaby Pharmaceuticals, Inc.
Crestwood, KY 40014

MG #27909

PRINCIPAL DISPLAY PANEL - 100 Tablet Bottle Label

NDC 35501-023-01

ZFLEX™

100 Tablets

Rx Only

Distributed by:
HUCKABY
Pharmaceuticals, Inc
Crestwood, KY 40014
Tel. 502-241-1570